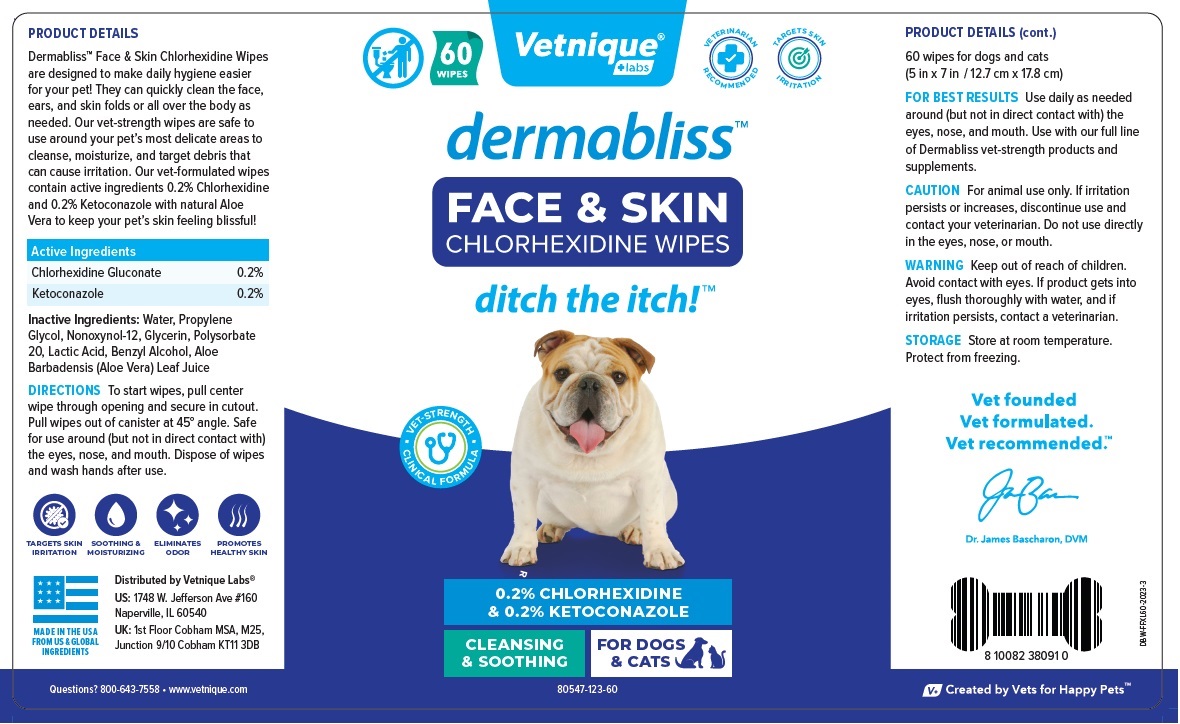 DRUG LABEL: dermabliss FACE and SKIN WIPES
NDC: 80547-123 | Form: CLOTH
Manufacturer: Vetnique Labs LLC
Category: animal | Type: OTC ANIMAL DRUG LABEL
Date: 20230814

ACTIVE INGREDIENTS: CHLORHEXIDINE GLUCONATE 2 mg/1 mL; KETOCONAZOLE 2 mg/1 mL
INACTIVE INGREDIENTS: WATER; PROPYLENE GLYCOL; NONOXYNOL-12; GLYCERIN; POLYSORBATE 20; LACTIC ACID, UNSPECIFIED FORM; BENZYL ALCOHOL; ALOE VERA LEAF

dermabliss™ FACE & SKIN CHLORHEXIDINE WIPES

Active Ingredients

Chlorhexidine Gluconate 0.2%
Ketoconazole 0.2%

INDICATIONS AND USAGE

PRODUCT DETAILS
Dermabliss™ Face & Skin Chlorhexidine Wipes are designed to make daily hygiene easier for your pet! They can quickly clean the face, ears, and skin folds or all over the body as needed. Our vet-strength wipes are safe to use around your pet’s most delicate areas to cleanse, moisturize, and target debris that can cause irritation. Our vet-formulated wipes contain active ingredients 0.2% Chlorhexidine and 0.2% Ketoconazole with natural Aloe Vera to keep your pet’s skin feeling blissful!

INACTIVE INGREDIENT

Inactive Ingredients: Water, Propylene Glycol, Nonoxynol-12, Glycerin, Polysorbate 20, Lactic Acid, Benzyl Alcohol, Aloe Barbadensis (Aloe Vera) Leaf Juice

DOSAGE AND ADMINISTRATION

DIRECTIONS To start wipes, pull center wipe through opening and secure in cutout. Pull wipes out of canister at 45° angle. Safe for use around (but not in direct contact with) the eyes, nose, and mouth. Dispose of wipes and wash hands after use.

FOR BEST RESULTS Use daily as needed around (but not in direct contact with) the eyes, nose, and mouth. Use with our full line of Dermabliss vet-strength products and supplements.

PRECAUTIONS

CAUTION For animal use only. If irritation persists or increases, discontinue use and contact your veterinarian. Do not use directly in the eyes, nose, or mouth.

WARNINGS

WARNING Keep out of reach of children. Avoid contact with eyes. If product gets into eyes, flush thoroughly with water, and if irritation persists, contact a veterinarian.

STORAGE Store at room temperature. Protect from freezing.

VETERINARIAN RECOMMENDED

TARGETS SKIN IRRITATION

ditch the itch!™

• VET-STRENGTH • CLINICAL FORMULA

CLEANSING & SOOTHING

FOR DOGS & CATS

Vet founded
Vet formulated.
Vet recommended.™

SOOTHING & MOISTURIZING

ELIMINATES ODOR

PROMOTES HEALTHY SKIN

MADE IN THE USA FROM US & GLOBAL INGREDIENTS

Distributed by Vetnique Labs®

US: 1748 W. Jefferson Ave #160
Naperville, IL 60540

UK: 1st Floor Cobham MSA, M25,
Junction 9/10 Cobham KT11 3DB

Questions? 800-643-7558 • www.vetnique.com

V+ Created by Vets for Happy Pets™